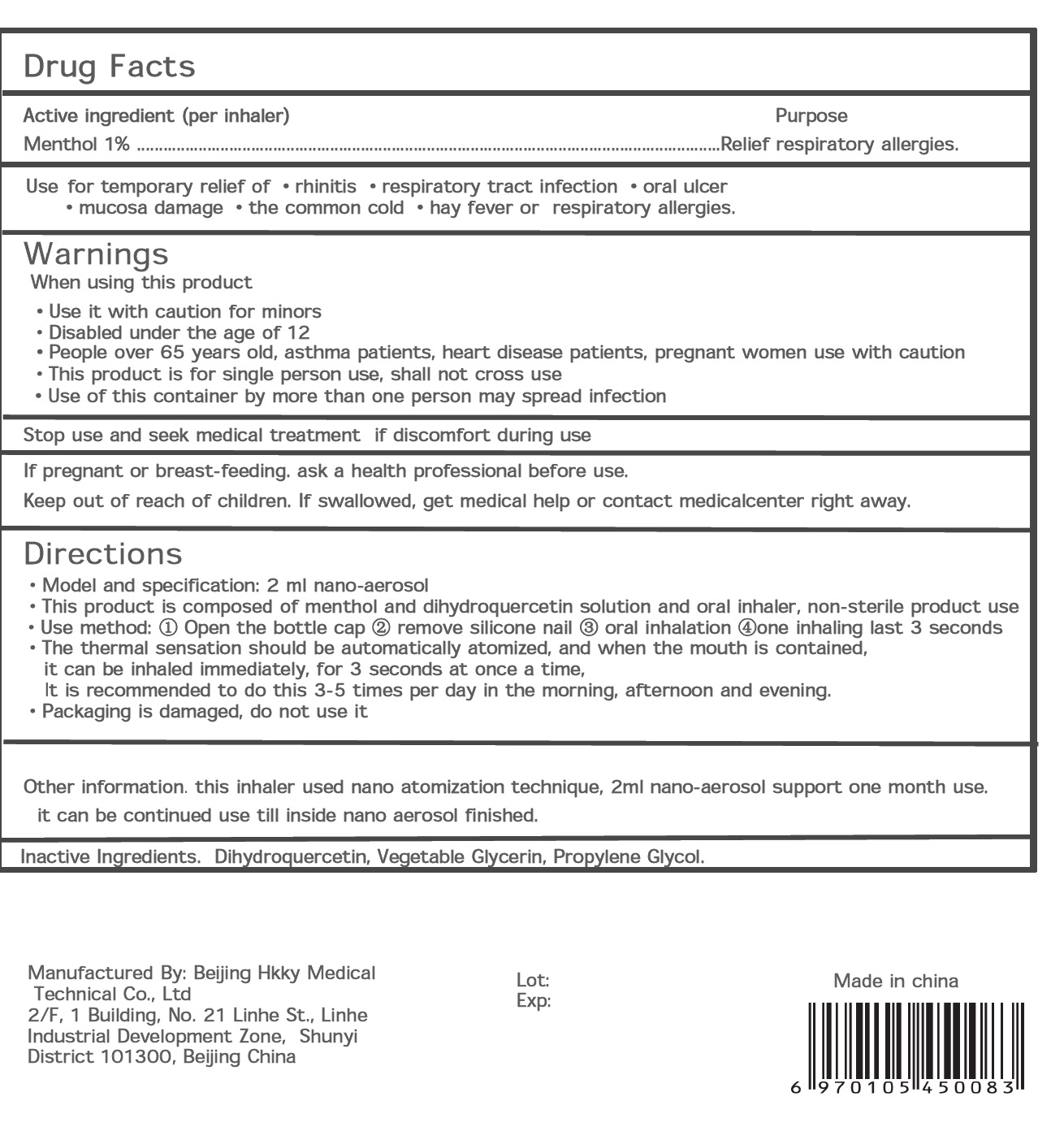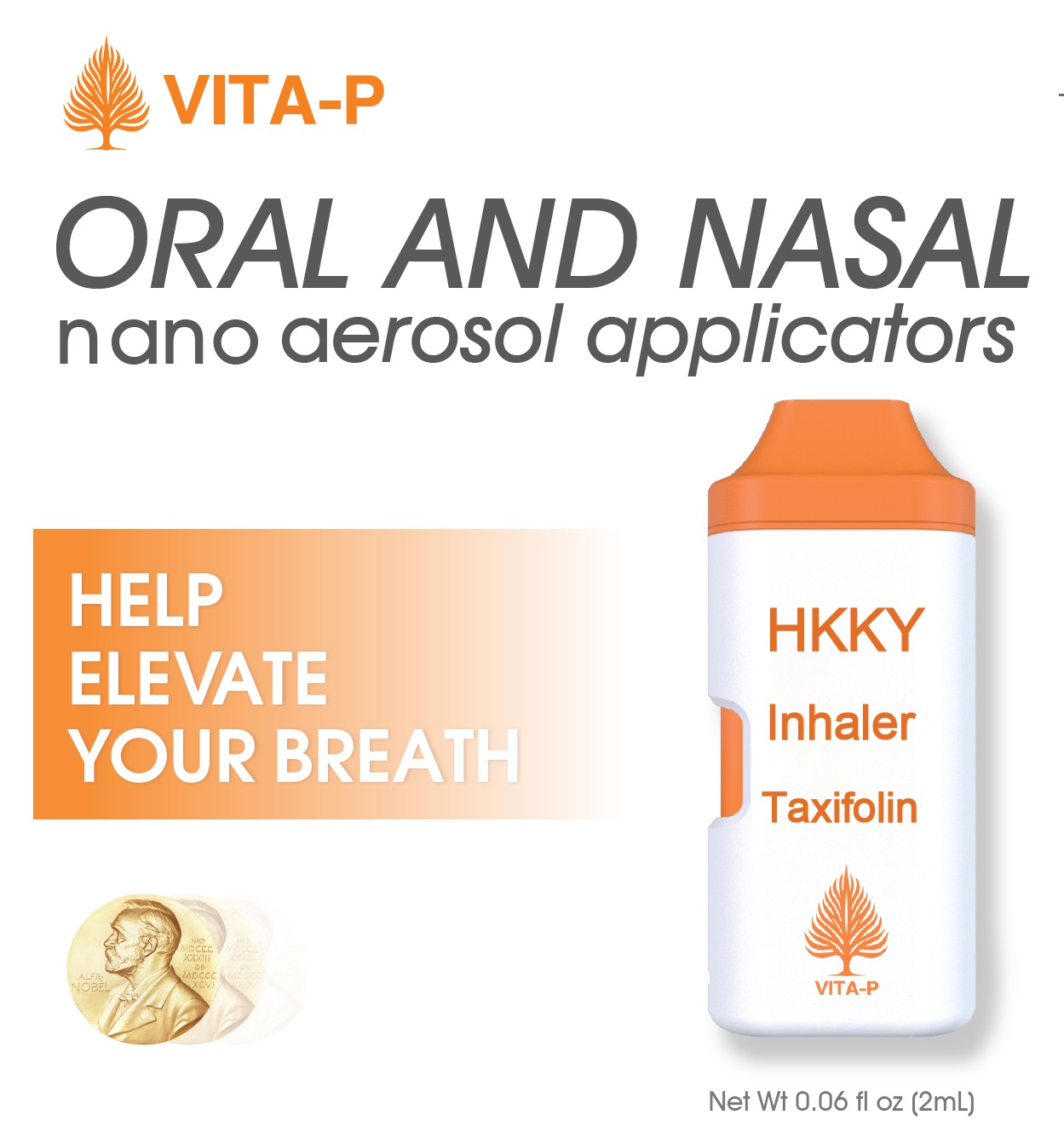 DRUG LABEL: Vita-P Oral and Nasal
NDC: 71073-308 | Form: AEROSOL, SPRAY
Manufacturer: Beijing HKKY Medical Tech. Co., Ltd.
Category: otc | Type: HUMAN OTC DRUG LABEL
Date: 20240113

ACTIVE INGREDIENTS: MENTHOL 0.01 g/1 g
INACTIVE INGREDIENTS: WATER; GLYCERIN; DIHYDROQUERCETIN GLUCOSIDE; PROPYLENE GLYCOL

71073-308, Vita-P Oral and Nasal

Active Ingredients

Menthol 1%

Purpose

Relief respiratory allergies

Uses

Use
·mucosa damage ·the common cold ·
for temporary relief of ·rhinitis ·respiratory tract infection ·oral ulcer
hay fever or respiratory allergies.

Warnings

If pregnant or breast-feeding. ask a health professional before use.

Do Not Use

Stop use and seek medical treatment if discomfort during use

When Using This Product

Use it with caution for minors
Stop use and seek medical treatment if discomfort during use
·People over 65 years old, asthma patients, heart disease patients, pregnant women use with caution
·Disabled under the age of 12
·This product is for single person use, shall not cross use
Use of this container by more than one person may spread infection

PREGNANCY OR BREAST FEEDING

If pregnant or breast-feeding. ask a health professional before use.

Keep Out of Reach of Children

If swallowed, get medical help or contact medicalcenter right away.

Other information

This inhaler used nano atomization technique, 2ml nano-aerosol support one month use.
it can be continued use till inside nano aerosol finished.

Directions

Model and specification: 2 ml nano-aerosol
·This product is composed of menthol and dihydroquercetin solution and oral inhaler, non-sterile product use

·Use method: ① Open the bottle cap ② remove silicone nail ③ oral inhalation ④one inhaling last 3 seconds
·The thermal sensation should be automatically atomized, and when the mouth is contained,
it can be inhaled immediately, for 3 seconds at once a time,
It is recommended to do this 3-5 times per day in the morning, afternoon and evening.
·Packaging is damaged, do not use it

Inactive Ingredients

Dihydroquercetin, Vegetable Glycerin, Propylene Glycol